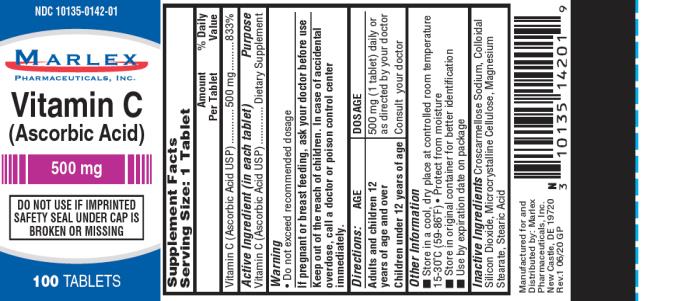 DRUG LABEL: Vitamin C
NDC: 10135-142 | Form: TABLET
Manufacturer: Marlex Pharmaceuticals Inc
Category: other | Type: DIETARY SUPPLEMENT
Date: 20200701

ACTIVE INGREDIENTS: ASCORBIC ACID 500 mg/1 1
INACTIVE INGREDIENTS: MICROCRYSTALLINE CELLULOSE; STEARIC ACID; SILICON DIOXIDE; MAGNESIUM STEARATE; CROSCARMELLOSE SODIUM

Vitamin C Ascorbic Acid Tablets

Supplement Facts

Serving Size: 1 Tablet
 | Amount per Tablet | % Daily Value
Vitamin C (Ascorbic Acid USP) | 500 mg | 833%
Active Ingredient (in each tablet) |  | Purpose
Vitamin C (Ascorbic Acid USP) |  | Dietary Supplement

Warning:

- Do not exceed recommended dosage.

If pregnant or breast-feeding,

ask your doctor before use.

Keep out of the reach of children.

In case of accidental overdose, call a doctor or poison control center immediately.

Directions

Adults and Children 12 years and over:

500 mg (1 tablet) daily or as directed by your doctor

Children under 12 years of age:

Consult your doctor

Other Information:

- Store in a cool, dry place at controlled room temperature 15-30ºC (59-86ºF)
- Protect from moisture
- Store in original container for better identification
- Use by expiration date on package

Inactive Ingredients:

Microcrystalline Cellulose, Stearic Acid, Colloidal Silicon Dioxide, Magnesium Stearate, Croscarmellose Sodium.

Manufactured for/Distributed by:
Marlex Pharmaceuticals, Inc.,
New Castle, DE 19720

Rev.1 6/20 GP

PRINCIPAL DISPLAY PANEL

NDC 10135-0142-01
Vitamin C
(Ascorbic Acid)
500mg
100 Tablets